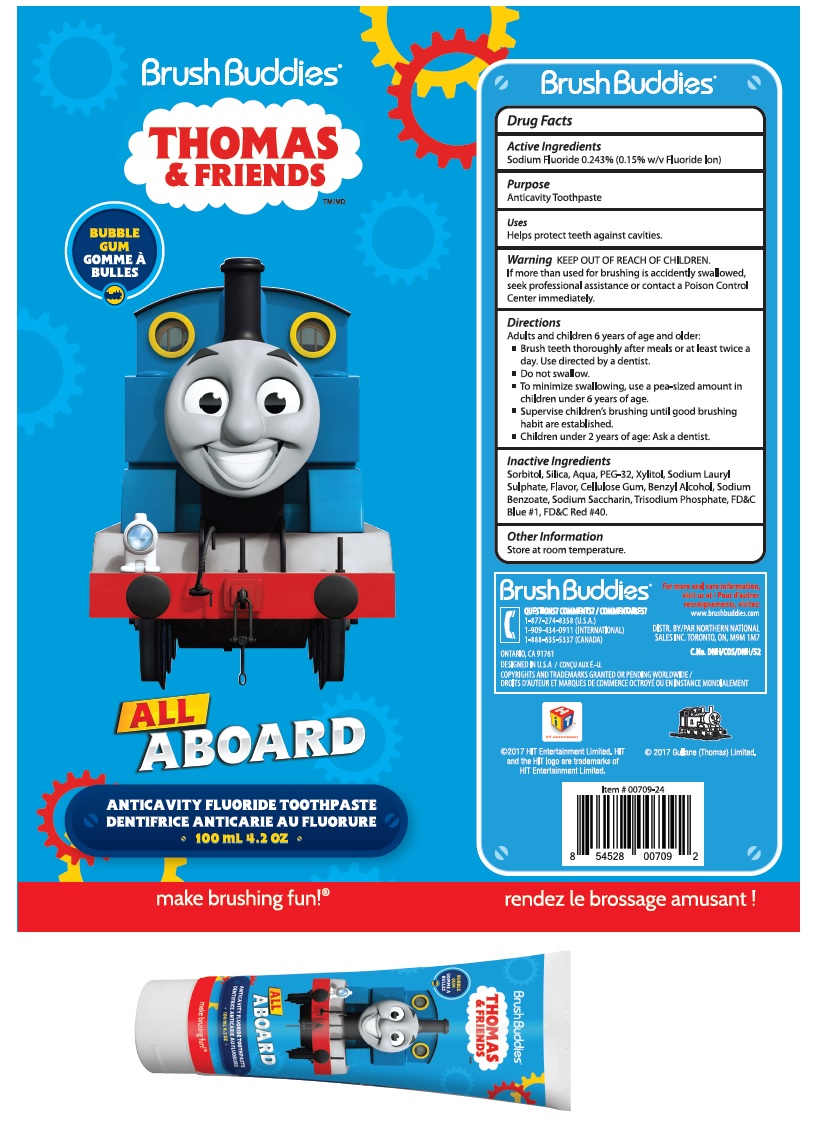 DRUG LABEL: Thomas and Friends
NDC: 70108-015 | Form: PASTE, DENTIFRICE
Manufacturer: Ashtel Studios, Inc.
Category: otc | Type: HUMAN OTC DRUG LABEL
Date: 20180516

ACTIVE INGREDIENTS: SODIUM FLUORIDE 243 mg/100 mL
INACTIVE INGREDIENTS: SORBITOL; SILICON DIOXIDE; WATER; POLYETHYLENE GLYCOL 1500; XYLITOL; SODIUM LAURYL SULFATE; CARBOXYMETHYLCELLULOSE SODIUM, UNSPECIFIED FORM; BENZYL ALCOHOL; SODIUM BENZOATE; SACCHARIN SODIUM; SODIUM PHOSPHATE, TRIBASIC, ANHYDROUS; FD&C BLUE NO. 1; FD&C RED NO. 40

Thomas & Friends Toothpaste

Active Ingredients

Sodium Fluoride 0.243% (0.15% w/v Fluoride Ion)

Purpose

Anticavity Toothpaste

Uses

Helps protect teeth against cavities.

KEEP OUT OF REACH OF CHILDREN

If more than used for brushing is accidently swallowed, seek professional assistance or contact a Poison Control Center immediately.

Directions

Adults and children 6 years of age and older:

- Brush teeth thoroughly after meals or at least twice a day. Use directed by a dentist.
- Do not swallow.
- To minimize swallowing, use a pea-sized amount in children under 6 years of age.
- Supervise children’s brushing until good brushing habit are established.
- Children under 2 years of age: Ask a dentist.

Inactive Ingredients

Sorbitol, Silica, Aqua, PEG-32, Xylitol, Sodium Lauryl Sulphate, Flavor, Cellulose Gum, Benzyl Alcohol, Sodium Benzoate, Sodium Saccharin, Trisodium Phosphate, FD&C Blue #1, FD&C Red #40.

Other Information

Store at room temperature.

QUESTIONS? COMMENTS? / COMMENTAIRES?
1-877-274-8358 (U.S.A.)
1-909-434-0911 (INTERNATIONAL)
1-888-635-5337 (CANADA)

BUBBLE GUM GOMME À BULLES

ANTICAVITY FLUORIDE TOOTHPASTE DENTIFRICE ANTICARIE AU FLUORURE

make brushing fun!®

For more oral care information,
visit us at / Pour d’autres
renseignements, visitez:
www.brushbuddies.com

DISTR. BY/PAR NORTHERN NATIONAL
SALES INC. TORONTO, ON, M9M 1M7

C.No. DNH/COS/DNH/52

©2017 HIT Entertainment Limited. HIT and the HIT logo are trademarks of HIT Entertainment Limited.

© 2017 Gullane (Thomas) Limited.